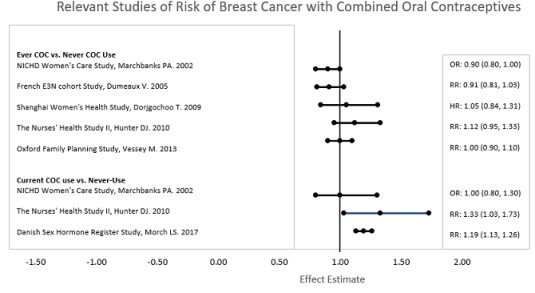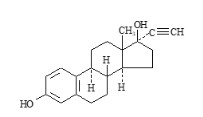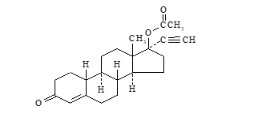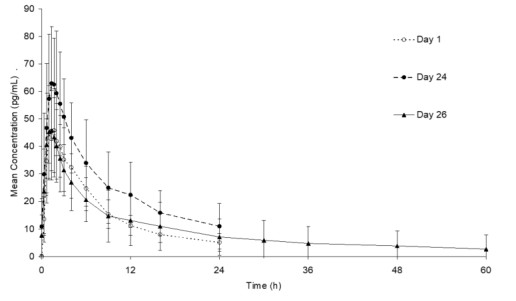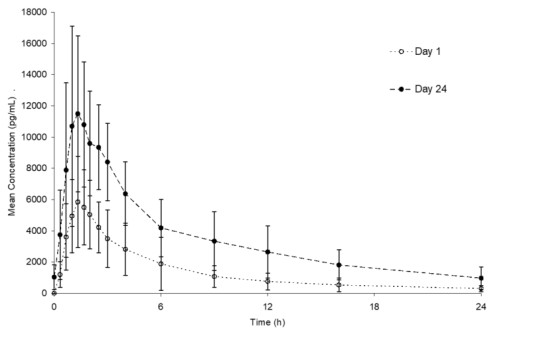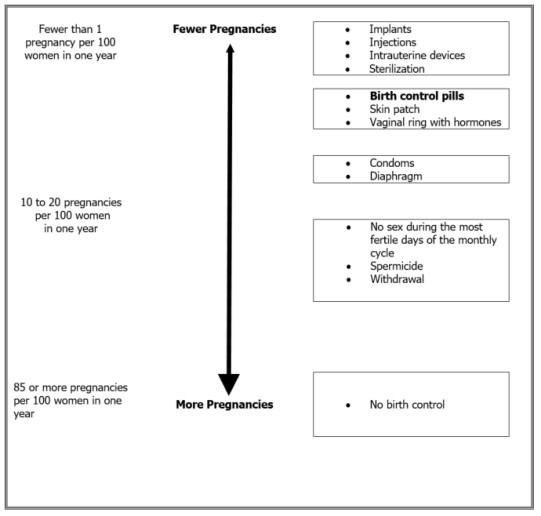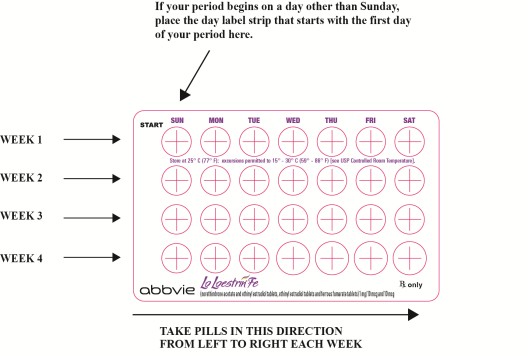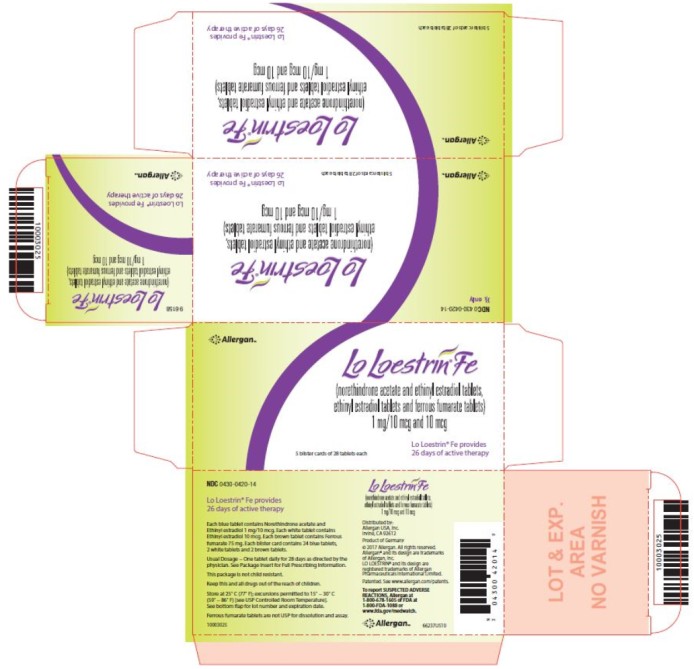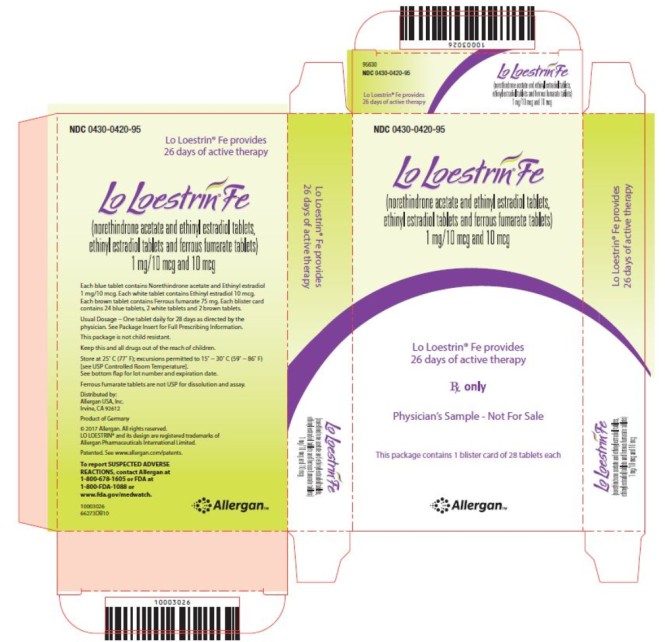 DRUG LABEL: Lo Loestrin Fe
NDC: 0430-0420 | Form: KIT | Route: ORAL
Manufacturer: Allergan, Inc.
Category: prescription | Type: HUMAN PRESCRIPTION DRUG LABEL
Date: 20250307

ACTIVE INGREDIENTS: NORETHINDRONE ACETATE 1 mg/1 1; ETHINYL ESTRADIOL 0.01 mg/1 1; ETHINYL ESTRADIOL 0.01 mg/1 1
INACTIVE INGREDIENTS: MANNITOL; MICROCRYSTALLINE CELLULOSE; FD&C BLUE NO. 1 ALUMINUM LAKE; SODIUM STARCH GLYCOLATE TYPE A; MAGNESIUM STEARATE; POVIDONE, UNSPECIFIED; ALPHA-TOCOPHEROL; LACTOSE MONOHYDRATE; MANNITOL; MICROCRYSTALLINE CELLULOSE; SODIUM STARCH GLYCOLATE TYPE A; MAGNESIUM STEARATE; POVIDONE, UNSPECIFIED; ALPHA-TOCOPHEROL; LACTOSE MONOHYDRATE; FERROUS FUMARATE 75 mg/1 1; MANNITOL; POVIDONE, UNSPECIFIED; MICROCRYSTALLINE CELLULOSE; SODIUM STARCH GLYCOLATE TYPE A; MAGNESIUM STEARATE; SUCRALOSE; SPEARMINT

HIGHLIGHTS OF PRESCRIBING INFORMATION

These highlights do not include all the information needed to use Lo Loestrin Fe safely and effectively. See full prescribing information for Lo Loestrin Fe.
Lo Loestrin® Fe (norethindrone acetate and ethinyl estradiol tablets, ethinyl estradiol tablets and ferrous fumarate tablets)
Initial U.S. Approval: 1968

RECENT MAJOR CHANGES

Warnings and Precautions (5.2) | 04/2022

WARNING: CIGARETTE SMOKING AND SERIOUS CARDIOVASCULAR EVENTS

See Full Prescribing Information for complete boxed warning.

- Women over 35 years old who smoke should not use Lo Loestrin Fe (4)
- Cigarette smoking increases the risk of serious cardiovascular events from combination oral contraceptive (COC) use (4)

1 INDICATIONS AND USAGE

- Lo Loestrin Fe is a combination of norethindrone acetate, a progestin, and ethinyl estradiol, an estrogen, indicated for use by women to prevent pregnancy (1)
- The efficacy of Lo Loestrin Fe in women with a body mass index of > 35 kg/m^2 has not been evaluated (1, 8.8)

2 DOSAGE AND ADMINISTRATION

- Take one tablet by mouth at the same time every day for 28 days (2.1)
- Take tablets in the order directed on the blister pack (2.1)

3 DOSAGE FORMS AND STRENGTHS

Lo Loestrin Fe consists of 28 tablets in the following order (3):

- 24 blue tablets (active), each containing 1 mg norethindrone acetate and 10 mcg ethinyl estradiol
- 2 white tablets (active), each containing 10 mcg ethinyl estradiol
- 2 brown tablets (non-hormonal placebo), each containing 75 mg ferrous fumarate. The ferrous fumarate tablets do not serve any therapeutic purpose

4 CONTRAINDICATIONS

- A high risk of arterial or venous thrombotic diseases (4)
- Breast cancer (4)
- Liver tumors or liver disease (4)
- Undiagnosed abnormal uterine bleeding (4)
- Co-administration with Hepatitis C drug combinations containing ombitasvir/paritaprevir/ritonavir, with or without dasabuvir (4)

5 WARNINGS AND PRECAUTIONS

- Vascular risks: Stop Lo Loestrin Fe if a thrombotic event occurs. Stop Lo Loestrin Fe at least 4 weeks before through 2 weeks after major surgery. Start Lo Loestrin Fe no earlier than 4 weeks after delivery, in women who are not breastfeeding (5.1)
- Liver disease: Discontinue Lo Loestrin Fe if jaundice occurs (5.3)
- High blood pressure: Do not prescribe Lo Loestrin Fe for women with uncontrolled hypertension or hypertension with vascular disease. (5.5)
- Carbohydrate and lipid metabolic effects: Monitor prediabetic and diabetic women taking Lo Loestrin Fe. Consider an alternative contraceptive method for women with uncontrolled dyslipidemia (5.7)
- Headache: Evaluate significant change in headaches and discontinue Lo Loestrin Fe if indicated (5.8)
- Uterine bleeding: Evaluate irregular bleeding or amenorrhea (5.9)

6 ADVERSE REACTIONS

The most common adverse reactions (≥ 2 percent) are nausea/vomiting (7 percent), headache (7 percent), bleeding irregularities (5 percent), dysmenorrhea (4 percent), weight change (4 percent), breast tenderness (4 percent), acne (3 percent), abdominal pain (3 percent), anxiety (2 percent) and depression (2 percent) (6)

To report SUSPECTED ADVERSE REACTIONS, contact AbbVie at 1-800-678-1605 or FDA at 1-800-FDA-1088 or www.fda.gov/medwatch.

7 DRUG INTERACTIONS

- Drugs or herbal products that induce certain enzymes, including CYP3A4, may decrease the effectiveness of COCs or increase breakthrough bleeding. Counsel patients to use a back-up method or alternative method of contraception when enzyme inducers are used with COCs (7.1)

-------------------USE IN SPECIFIC POPULATIONS---------------------

- Lactation: Not recommended; Lo Loestrin Fe can decrease milk production (8.2)

FULL PRESCRIBING INFORMATION

WARNING: CIGARETTE SMOKING AND SERIOUS CARDIOVASCULAR EVENTS

Cigarette smoking increases the risk of serious cardiovascular events from combination oral contraceptive (COC) use. This risk increases with age, particularly in women over 35 years of age, and with the number of cigarettes smoked. For this reason, COCs should not be used by women who are over 35 years of age and smoke [see Contraindications (4)].

1 INDICATIONS AND USAGE

Lo Loestrin® Fe is indicated for use by women to prevent pregnancy [see Clinical Studies (14)].

The efficacy of Lo Loestrin Fe in women with a body mass index (BMI) of > 35 kg/m^2 has not been evaluated.

2 DOSAGE AND ADMINISTRATION

2.1 How to Take Lo Loestrin Fe

To achieve maximum contraceptive effectiveness, Lo Loestrin Fe must be taken exactly as directed. Take one tablet by mouth at the same time every day. Tablets must be taken in the order directed on the blister pack. Tablets should not be skipped or taken at intervals exceeding 24 hours. Lo Loestrin Fe tablets may be administered without regard to meals [see Clinical Pharmacology (12.3)].

2.2 How to Start Lo Loestrin Fe

Instruct the patient to begin taking Lo Loestrin Fe on Day 1 of her menstrual cycle (that is, the first day of her menstrual bleeding). One blue tablet should be taken daily for 24 consecutive days, followed by one white tablet daily for 2 consecutive days, followed by one brown tablet daily for 2 consecutive days. Instruct the patient to use a non-hormonal contraceptive as back-up during the first 7 days if she starts taking Lo Loestrin Fe other than on the first day of her menstrual cycle.

For postpartum women who do not breastfeed or after a second trimester abortion, Lo Loestrin Fe may be started no earlier than 4 weeks postpartum. Recommend use of a non-hormonal back-up method for the first 7 days. When COCs are used during the postpartum period, the increased risk of thromboembolic disease associated with the postpartum period must be considered [see Warnings and Precautions (5.1)]. The possibility of ovulation and conception before starting COCs should also be considered.

Lo Loestrin Fe may be initiated immediately after a first-trimester abortion or miscarriage; if the patient starts Lo Loestrin Fe immediately, additional contraceptive measures are not needed.

2.3 Switching from another Hormonal Method of Contraception

If the patient is switching from a combination hormonal method such as:

○ Another pill
○ Vaginal ring
○ Patch

- Instruct her to take the first blue tablet on the day she would have taken her next COC pill. She should not continue taking the tablets from her previous birth control pack and should not skip any days between packs. If she does not have a withdrawal bleed, rule out pregnancy before starting Lo Loestrin Fe.
- If she previously used a vaginal ring or transdermal patch, she should start using Lo Loestrin Fe on the day she would have resumed the previous product.

If the patient is switching from a progestin-only method such as a:

○ Progestin-only pill
○ Implant
○ Intrauterine system
○ Injection

- Instruct her to take the first blue tablet on the day she would have taken her next progestin-only pill, or had her next injection or on the day of removal of her implant.
- If switching from an IUD, depending on the timing of removal, back-up contraception may be needed.

2.4 Missed Doses

Table 1: Instructions for Missed Lo Loestrin Fe Tablets in a Monthly Dosing Regimen

- If one blue tablet is missed | Take the tablet as soon as possible, even if two tablets are taken in one day. Continue taking one tablet a day until the pack is finished.
- If two consecutive blue tablets are missed in Week 1 or Week 2 | Take the two missed tablets as soon as possible, and the next two tablets the next day. Continue taking the remaining tablets, one tablet a day until the pack is finished. Use additional non-hormonal contraception (such as condoms and spermicide) for 7 consecutive days after missing tablets.
- If two consecutive tablets (blue or white) are missed in Week 3 or Week 4 | Throw out the rest of the pack and start a new pack the same day. A withdrawal bleed may not occur. Use additional non-hormonal contraception (such as condoms and spermicide) for 7 consecutive days after missing tablets.
- If three or more consecutive tablets (blue or white) are missed at any time | Throw out the rest of the pack and start a new pack that same day. A withdrawal bleeding may not occur. Use additional non-hormonal contraception (such as condoms and spermicide) for 7 consecutive days after missing tablets.
- If either of the brown tablets in Week 4 are missed | Throw out the tablet you missed. Start a new pack on the same day a new pack is usually started.

2.5 Advice in Case of Gastrointestinal Disturbances

If the patient vomits or has diarrhea (within 3 to 4 hours after she takes a blue or white pill), she should follow the instructions in Missed Doses [see Dosage and Administration (2.4)].

3 DOSAGE FORMS AND STRENGTHS

Lo Loestrin Fe (norethindrone acetate and ethinyl estradiol tablets, ethinyl estradiol tablets and ferrous fumarate tablets) is available in blister packs.

Each blister pack (28 tablets) contains in the following order:

- 24 blue, round (active) tablets imprinted with “WC” on one side and “421” on the other and each containing 1 mg norethindrone acetate and 10 mcg ethinyl estradiol.
- 2 white, hexagonal (active) tablets imprinted with “WC” on one side and “422” on the other and each containing 10 mcg ethinyl estradiol.
- 2 brown, round (non-hormonal placebo) tablets imprinted with “WC” on one side and “624” on the other and each containing 75 mg ferrous fumarate. The ferrous fumarate tablets do not serve any therapeutic purpose.

4 CONTRAINDICATIONS

Lo Loestrin Fe is contraindicated in females who are known to have or develop the following conditions:

- A high risk of arterial or venous thrombotic diseases. Examples include women who are known to:
  • Smoke, if over age 35 [see Boxed Warning and Warnings and Precautions (5.1)]
  • Have deep vein thrombosis or pulmonary embolism, now or in the past [see Warnings and Precautions (5.1)]
  • Have cerebrovascular disease [see Warnings and Precautions (5.1)]
  • Have coronary artery disease [see Warnings and Precautions (5.1)]
  • Have thrombogenic valvular or thrombogenic rhythm diseases of the heart (for example, subacute bacterial endocarditis with valvular disease, or atrial fibrillation) [see Warnings and Precautions (5.1)]
  • Have inherited or acquired hypercoagulopathies [see Warnings and Precautions (5.1)]
  • Have uncontrolled hypertension [see Warnings and Precautions (5.5)]
  • Have diabetes mellitus with vascular disease [see Warnings and Precautions (5.7)]
  • Have headaches with focal neurological symptoms or have migraine headaches with or without aura if over age 35 [see Warnings and Precautions (5.8)]
- Current diagnosis of, or history of, breast cancer, which may be hormone-sensitive [see Warnings and Precautions (5.2)]
- Liver tumors, benign or malignant, or liver disease [see Warnings and Precautions (5.3)]
- Undiagnosed abnormal uterine bleeding [see Warnings and Precautions (5.9)]
- Use of Hepatitis C drug combinations containing ombitasvir/paritaprevir/ritonavir, with or without dasabuvir, due to the potential for ALT elevations [see Warnings and Precautions (5.4)].

5 WARNINGS AND PRECAUTIONS

5.1 Thrombotic and Other Vascular Events

Stop Lo Loestrin Fe if an arterial or deep venous thrombotic event occurs. Although use of COCs increases the risk of venous thromboembolism, pregnancy increases the risk of venous thromboembolism as much or more than the use of COCs. The risk of venous thromboembolism in women using COCs is 3 to 9 per 10,000 woman-years. The risk is highest during the first year of use of a COC. Use of COCs also increases the risk of arterial thromboses such as strokes and myocardial infarctions, especially in women with other risk factors for these events. The risk of thromboembolic disease due to oral contraceptives gradually disappears after COC use is discontinued.

If feasible, stop Lo Loestrin Fe at least 4 weeks before and through 2 weeks after major surgery or other surgeries known to have an elevated risk of thromboembolism.

Start Lo Loestrin Fe no earlier than 4 weeks after delivery, in women who are not breastfeeding. The risk of postpartum thromboembolism decreases after the third postpartum week, whereas the risk of ovulation increases after the third postpartum week.

COCs have been shown to increase both the relative and attributable risks of cerebrovascular events (thrombotic and hemorrhagic strokes), although, in general, the risk is greatest in older (> 35 years of age), hypertensive women who also smoke. COCs also increase the risk for stroke in women with underlying risk factors.

Oral contraceptives must be used with caution in women with cardiovascular disease risk factors.

Stop Lo Loestrin Fe if there is unexplained loss of vision, proptosis, diplopia, papilledema, or retinal vascular lesions. Evaluate for retinal vein thrombosis immediately.

5.2 Malignant Neoplasms

Breast Cancer
Lo Loestrin Fe is contraindicated in females who currently have or have had breast cancer because breast cancer may be hormonally sensitive [see Contraindications (4)].
Epidemiology studies have not found a consistent association between use of combined oral contraceptives (COCs) and breast cancer risk. Studies do not show an association between ever (current or past) use of COCs and risk of breast cancer. However, some studies report a small increase in the risk of breast cancer among current or recent users (<6 months since last use) and current users with longer duration of COC use [see Adverse Reactions (6.2)].

Cervical Cancer

Some studies suggest that COCs are associated with an increase in the risk of cervical cancer or intraepithelial neoplasia. However, there is controversy about the extent to which these findings may be due to differences in sexual behavior and other factors.

5.3 Liver Disease

Discontinue Lo Loestrin Fe if jaundice develops. Steroid hormones may be poorly metabolized in patients with impaired liver function. Acute or chronic disturbances of liver function may necessitate the discontinuation of COC use until markers of liver function return to normal and COC causation has been excluded.

Hepatic adenomas are associated with COC use. An estimate of the attributable risk is 3.3 cases per 100,000 COC users. Rupture of hepatic adenomas may cause death through intra-abdominal hemorrhage.

Studies have shown an increased risk of developing hepatocellular carcinoma in long-term (>8 years) COC users. However, the attributable risk of liver cancers in COC users is less than one case per million users.

Oral contraceptive-related cholestasis may occur in women with a history of pregnancy-related cholestasis. Women with a history of COC-related cholestasis may have the condition recur with subsequent COC use.

5.4 Risk of Liver Enzyme Elevations with Concomitant Hepatitis C Treatment

During clinical trials with the Hepatitis C combination drug regimen that contains ombitasvir/paritaprevir/ritonavir, with or without dasabuvir, ALT elevations greater than 5 times the upper limit of normal (ULN), including some cases greater than 20 times the ULN, were significantly more frequent in women using ethinyl estradiol-containing medications, such as COCs. Discontinue Lo Loestrin Fe prior to starting therapy with the combination drug regimen ombitasvir/paritaprevir/ritonavir, with or without dasabuvir [see Contraindications (4)]. Lo Loestrin Fe can be restarted approximately 2 weeks following completion of treatment with the Hepatitis C combination drug regimen.

5.5 High Blood Pressure

For women with well-controlled hypertension, monitor blood pressure and stop Lo Loestrin Fe if blood pressure rises significantly. Women with uncontrolled hypertension or hypertension with vascular disease should not use COCs.

An increase in blood pressure has been reported in women taking COCs, and this increase is more likely in older women with extended duration of use. The incidence of hypertension increases with increasing concentrations of progestin.

5.6 Gallbladder Disease

Studies suggest a small increased relative risk of developing gallbladder disease among COC users.

5.7 Carbohydrate and Lipid Metabolic Effects

Carefully monitor prediabetic and diabetic women who are taking Lo Loestrin Fe. COCs may decrease glucose tolerance in a dose-related fashion.

Consider alternative contraception for women with uncontrolled dyslipidemias. A small proportion of women will have adverse lipid changes while on COCs.

Women with hypertriglyceridemia, or a family history thereof, may be at an increased risk of pancreatitis when using COCs.

5.8 Headache

If a woman taking Lo Loestrin Fe develops new headaches that are recurrent, persistent, or severe, evaluate the cause and discontinue Lo Loestrin Fe if indicated.

An increase in frequency or severity of migraine during COC use (which may be prodromal of a cerebrovascular event) may be a reason for immediate discontinuation of the COC.

5.9 Bleeding Irregularities and Amenorrhea

Unscheduled (breakthrough or intracyclic) bleeding and spotting sometimes occur in patients on COCs, especially during the first three months of use. If bleeding persists or occurs after previously regular cycles, check for causes such as pregnancy or malignancy. If pathology and pregnancy are excluded, bleeding irregularities may resolve over time or with a change to a different COC.

The clinical trial that evaluated the efficacy of Lo Loestrin Fe also assessed unscheduled bleeding and/or spotting. The participants in this 12-month clinical trial (N = 1,582 who had at least one post-treatment evaluation) completed over 15,000 cycles of exposure.

A total of 1,257 women (85.9 percent) experienced unscheduled bleeding and/or spotting at some time during Cycles 2 to 13 of this study. The incidence of unscheduled bleeding and/or spotting was highest during Cycle 2 (53 percent) and lowest at Cycle 13 (36 percent). Among these women, the mean number of days of unscheduled bleeding and/or spotting during a 28-day cycle ranged from 1.8 to 3.2 days.

Scheduled (withdrawal) bleeding and/or spotting remained fairly constant over the one year study, with an average of less than 2 days per cycle.

Women who are not pregnant and use Lo Loestrin Fe may experience amenorrhea (absence of scheduled and unscheduled bleeding/spotting). In the clinical trial with Lo Loestrin Fe, the incidence of amenorrhea increased from 32 percent in Cycle 1 to 49 percent by Cycle 13. If scheduled (withdrawal) bleeding does not occur, consider the possibility of pregnancy. If the patient has not adhered to the prescribed dosing schedule (missed one or more active tablets or started taking them on a day later than she should have), consider the possibility of pregnancy at the time of the first missed period and take appropriate diagnostic measures. If the patient has adhered to the prescribed regimen and misses two consecutive periods, rule out pregnancy.

Some women may experience amenorrhea or oligomenorrhea after stopping COCs, especially when such a condition was preexistent.

5.10 COC Use before or during Early Pregnancy

Extensive epidemiologic studies have revealed no increased risk of birth defects in women who have used oral contraceptives prior to pregnancy. Studies also do not suggest a teratogenic effect, particularly in so far as cardiac anomalies and limb reduction defects are concerned, when oral contraceptives are taken inadvertently during early pregnancy. Lo Loestrin Fe use should be discontinued if pregnancy is confirmed.

Administration of oral contraceptives to induce withdrawal bleeding should not be used as a test for pregnancy [see Use in Specific Populations (8.1)].

5.11 Depression

Women with a history of depression should be carefully observed and Lo Loestrin Fe discontinued if depression recurs to a serious degree.

5.12 Interference with Laboratory Tests

The use of COCs may change the results of some laboratory tests, such as coagulation factors, lipids, glucose tolerance, and binding proteins. Women on thyroid hormone replacement therapy may need increased doses of thyroid hormone because serum concentrations of thyroid binding globulin increase with use of COCs.

5.13 Monitoring

A woman who is taking COCs should have a yearly visit with her healthcare provider for a blood pressure check and for other indicated healthcare.

5.14 Other Conditions

In women with hereditary angioedema, exogenous estrogens may induce or exacerbate symptoms of angioedema. Chloasma may occasionally occur, especially in women with a history of chloasma gravidarum. Women with a tendency to chloasma should avoid exposure to the sun or ultraviolet radiation while taking COCs.

6 ADVERSE REACTIONS

The following serious adverse reactions with the use of COCs are discussed elsewhere in the labeling:

- Serious cardiovascular events and smoking [see Boxed Warning and Warnings and Precautions (5.1)]
- Vascular events [see Warnings and Precautions (5.1)]
- Liver disease [see Warnings and Precautions (5.3)]

Adverse reactions commonly reported by COC users are:

- Irregular uterine bleeding
- Nausea
- Breast tenderness
- Headache

6.1 Clinical Trial Experience

Because clinical trials are conducted under widely varying conditions, adverse reaction rates observed in the clinical trials of a drug cannot be directly compared to the rates in the clinical trials of another drug and may not reflect the rates observed in practice.

A multicenter phase 3 clinical trial evaluated the safety and efficacy of Lo Loestrin Fe for pregnancy prevention. The study was a one year, open-label, single-arm, uncontrolled study. A total of 1,660 women aged 18 to 45 were enrolled and took at least one dose of Lo Loestrin Fe [see Clinical Studies (14)].

Common Adverse Reactions (≥ 2 percent of all Treated Subjects): The most common adverse reactions reported by at least 2 percent of the 1,660 women using Lo Loestrin Fe were the following in order of decreasing incidence: nausea/vomiting (7 percent), headache (7 percent), bleeding irregularities (including metrorrhagia, irregular menstruation, menorrhagia, vaginal hemorrhage and dysfunctional uterine bleeding) (5 percent), dysmenorrhea (4 percent), weight fluctuation (4 percent), breast tenderness (4 percent), acne (3 percent), abdominal pain (3 percent), anxiety (2 percent), and depression (2 percent).

Adverse Reactions Leading to Study Discontinuation: 10.7 percent of the women discontinued from the clinical trial due to an adverse reaction. Adverse reactions occurring in ≥1 percent of subjects leading to discontinuation of treatment were in decreasing order: menstrual irregularities (including metrorrhagia, irregular menstruation, menorrhagia and vaginal hemorrhage) (4 percent), headache/migraine (1 percent), mood disorder (including mood swings, depression, anxiety) (1 percent), and weight fluctuation (1 percent).

Serious Adverse Reactions: deep vein thrombosis, ovarian vein thrombosis, cholecystitis.

6.2 Postmarketing Experience

Five studies that compared breast cancer risk between ever-users (current or past use) of COCs and never-users of COCs reported no association between ever use of COCs and breast cancer risk, with effect estimates ranging from 0.90 - 1.12 (Figure 1).

Three studies compared breast cancer risk between current or recent COC users (<6 months since last use) and never users of COCs (Figure 1). One of these studies reported no association between breast cancer risk and COC use. The other two studies found an increased relative risk of 1.19 - 1.33 with current or recent use. Both of these studies found an increased risk of breast cancer with current use of longer duration, with relative risks ranging from 1.03 with less than one year of COC use to approximately 1.4 with more than 8-10 years of COC use.

Figure 1.

RR = relative risk; OR = odds ratio; HR = hazard ratio. “ever COC” are females with current or past COC use; “never COC use” are females that never used COCs.

7 DRUG INTERACTIONS

No drug-drug interaction studies were conducted with Lo Loestrin Fe.

7.1 Changes in Contraceptive Effectiveness Associated with Co-Administration of Other Products

If a woman on hormonal contraceptives takes a drug or herbal product that induces enzymes, including CYP3A4, that metabolize contraceptive hormones, counsel her to use additional contraception or a different method of contraception. Drugs or herbal products that induce such enzymes may decrease the plasma concentrations of contraceptive hormones, and may decrease the effectiveness of hormonal contraceptives or increase breakthrough bleeding. Some drugs or herbal products that may decrease the effectiveness of hormonal contraceptives include:

- barbiturates
- bosentan
- carbamazepine
- felbamate
- griseofulvin
- oxcarbazepine
- phenytoin
- rifampin
- St. John’s wort
- topiramate

HIV protease inhibitors and non-nucleoside reverse transcriptase inhibitors: Significant changes (increase or decrease) in the plasma levels of the estrogen and progestin have been noted in some cases of co-administration of HIV protease inhibitors or of non-nucleoside reverse transcriptase inhibitors.

Antibiotics: There have been reports of pregnancy while taking hormonal contraceptives and antibiotics, but clinical pharmacokinetic studies have not shown consistent effects of antibiotics on plasma concentrations of synthetic steroids.

Consult the labeling of all concurrently-used drugs to obtain further information about interactions with hormonal contraceptives or the potential for enzyme alterations.

7.2 Increase in Plasma Levels of Ethinyl Estradiol Associated with Co-Administered Drugs

Co-administration of atorvastatin and certain COCs containing ethinyl estradiol increase AUC values for ethinyl estradiol by approximately 20 percent. Ascorbic acid and acetaminophen may increase plasma ethinyl estradiol levels, possibly by inhibition of conjugation. CYP3A4 inhibitors such as itraconazole or ketoconazole may increase plasma hormone levels.

7.3 Concomitant Use with HCV Combination Therapy – Liver Enzyme Elevation

Do not co-administer Lo Loestrin Fe with HCV drug combinations containing ombitasvir/ paritaprevir/ritonavir, with or without dasabuvir, due to potential for ALT elevations [see Warnings and Precautions (5.4)].

7.4 Changes in Plasma Levels of Co-Administered Drugs

COCs containing some synthetic estrogens (for example, ethinyl estradiol) may inhibit the metabolism of other compounds. COCs have been shown to significantly decrease plasma concentrations of lamotrigine, likely due to induction of lamotrigine glucuronidation. This may reduce seizure control; therefore, dosage adjustments of lamotrigine may be necessary. Consult the labeling of the concurrently-used drug to obtain further information about interactions with COCs or the potential for enzyme alterations.

8 USE IN SPECIFIC POPULATIONS

8.1 Pregnancy

Risk Summary

There is no use for contraception in pregnancy; therefore, Lo Loestrin Fe should be discontinued during pregnancy. Epidemiologic studies and meta-analyses have not found an increased risk of genital or nongenital birth defects (including cardiac anomalies and limb reduction defects) following exposure to combined hormonal contraceptives (CHCs) before conception or during early pregnancy.

In the U.S. general population, the estimated background risk of major birth defects and miscarriage in clinically recognized pregnancies is 2 to 4 percent and 15 to 20 percent, respectively.

Data

Human Data

Epidemiologic studies and meta-analyses have not found an increased risk of genital or nongenital birth defects (including cardiac anomalies and limb-reduction defects) following exposure to CHCs before conception or during early pregnancy.

8.2 Lactation

Risk Summary

Contraceptive hormones and/or metabolites are present in human milk. CHCs can reduce milk production in breastfeeding females. This reduction can occur at any time but is less likely to occur once breastfeeding is well-established. When possible, advise the nursing female to use other methods of contraception until she discontinues breastfeeding. [See also Dosage and Administration (2.2).] The developmental and health benefits of breastfeeding should be considered along with the mother’s clinical need for Lo Loestrin Fe and any potential adverse effects on the breastfed child from Lo Loestrin Fe or from the underlying maternal condition.

8.4 Pediatric Use

Safety and efficacy of Lo Loestrin Fe have been established in women of reproductive age. Safety and efficacy are expected to be the same in postpubertal adolescents under the age of 18 years as for users 18 years and older. Use of this product before menarche is not indicated.

8.5 Geriatric Use

Lo Loestrin Fe has not been studied in postmenopausal women and is not indicated in this population.

8.6 Renal Impairment

The pharmacokinetics of Lo Loestrin Fe has not been studied in subjects with renal impairment.

8.7 Hepatic Impairment

No studies have been conducted to evaluate the effect of hepatic impairment on the disposition of Lo Loestrin Fe. However, steroid hormones may be poorly metabolized in patients with impaired liver function. Acute or chronic disturbances of liver function may necessitate the discontinuation of COC use until markers of liver function return to normal and COC causation has been excluded [see Contraindications (4) and Warnings and Precautions (5.3)].

8.8 Body Mass Index

The safety and efficacy of Lo Loestrin Fe in women with a body mass index (BMI) >35 kg/m^2 has not been evaluated [see Clinical Studies (14)].

10 OVERDOSAGE

There have been no reports of serious ill effects from overdose of oral contraceptives, including ingestion by children. Overdosage may cause withdrawal bleeding in females and nausea.

11 DESCRIPTION

Lo Loestrin Fe (norethindrone acetate and ethinyl estradiol tablets, ethinyl estradiol tablets and ferrous fumarate tablets) provides an oral contraceptive regimen consisting of 24 blue active tablets and 2 white active tablets that contain the active ingredients specified for each tablet below, followed by 2 non-hormonal placebo tablets:

- 24 blue, round tablets each containing 1 mg norethindrone acetate and 10 mcg ethinyl estradiol
- 2 white, hexagonal tablets each containing 10 mcg ethinyl estradiol
- 2 brown, round tablets each containing 75 mg ferrous fumarate

Each blue tablet also contains the inactive ingredients mannitol, microcrystalline cellulose, FD&C Blue No. 1 Aluminum Lake, sodium starch glycolate, magnesium stearate, povidone, vitamin E and lactose monohydrate.

Each white tablet also contains the inactive ingredients mannitol, microcrystalline cellulose, sodium starch glycolate, magnesium stearate, povidone, vitamin E and lactose monohydrate.

Each brown tablet contains ferrous fumarate, mannitol, povidone, microcrystalline cellulose, sodium starch glycolate, magnesium stearate, sucralose and spearmint flavor. The ferrous fumarate tablets do not serve any therapeutic purpose. Ferrous fumarate tablets are not USP for dissolution and assay.

The empirical formula of ethinyl estradiol is C20H24O2 and the structural formula is:

The chemical name of ethinyl estradiol is [19-Norpregna-1,3,5(10)-trien-20-yne-3,17-diol, (17α)-].

The empirical formula of norethindrone acetate is C22H28O3 and the structural formula is:

The chemical name of norethindrone acetate is [19-Norpregn-4-en-20-yn-3-one, 17-(acetyloxy)-, (17α)-].

12 CLINICAL PHARMACOLOGY

12.1 Mechanism of Action

CHCs prevent pregnancy primarily by suppressing ovulation.

12.2 Pharmacodynamics

No specific pharmacodynamic studies were conducted with Lo Loestrin Fe.

12.3 Pharmacokinetics

Absorption

Norethindrone acetate is deacetylated to norethindrone after oral administration, and the disposition of norethindrone acetate is indistinguishable from that of orally administered norethindrone. Norethindrone acetate and ethinyl estradiol are absorbed from Lo Loestrin Fe, with maximum plasma concentrations of norethindrone and ethinyl estradiol generally occurring 1 to 2 hours postdose. Both are subject to first-pass metabolism after oral dosing, resulting in an absolute bioavailability of approximately 64 percent for norethindrone and 55 percent for ethinyl estradiol.

The rate of norethindrone and ethinyl estradiol absorption from Lo Loestrin Fe tablets containing the combination of 1 mg norethindrone acetate and 10 mcg ethinyl estradiol is slower than that from a norethindrone suspension/ethinyl estradiol solution, but the extent of absorption is equivalent.

Ethinyl estradiol bioavailability from Lo Loestrin Fe tablets containing 10 mcg ethinyl estradiol alone is equivalent to that from an ethinyl estradiol solution.

The plasma norethindrone and ethinyl estradiol pharmacokinetic profiles and serum sex hormone binding globulin (SHBG) concentrations following multiple-dose administration of Lo Loestrin Fe were characterized in 15 healthy female volunteers. The mean plasma concentrations are shown below (Figures 2 and 3), and pharmacokinetic parameters are found in Table 2.

Ethinyl estradiol and norethindrone Cmax values increase by a factor of 1.4 and 1.9, respectively, following 24 days administration of Lo Loestrin Fe combination tablets as compared to single-dose administration. Ethinyl estradiol and norethindrone AUC0–24h values increase by a factor of 1.6 and 2.5, respectively, following 24 days administration of Lo Loestrin Fe combination tablets as compared to single-dose administration. Norethindrone concentrations more than double by Day 24 due to both accumulation and increased SHBG concentration. Steady state with respect to ethinyl estradiol and norethindrone is reached by Day 5 and Day 13, respectively.

Figure 2. Mean (± SD) plasma ethinyl estradiol concentration versus time profiles following single- and multiple-dose oral administration of Lo Loestrin Fe to healthy female volunteers (n = 15)

Figure 3. Mean (± SD) plasma norethindrone concentration versus time profiles following single- and multiple-dose oral administration of Lo Loestrin Fe to healthy female volunteers (n = 15)

Table 2. Summary of Norethindrone (NE) and Ethinyl Estradiol (EE) Pharmacokinetic Parameter Values Following Oral Administration of Lo Loestrin Fe to Healthy Female Volunteers (n = 15)

Regimen | Study Day |  | Arithmetic Meana (Percent CV) by Pharmacokinetic Parameter
 |  | Analyte | Cmax | tmax | AUC0-24h | Cmin | Cavg
Single Dose Lo Loestrin Fe combination tabletc | 1 | NE | 7360 (21) | 1.7 (1.3-6.0) | 33280 (33) | -- | --
 |  | EE | 50.9 (27) | 1.3 (1.0-6.0) | 389.9 (27) | -- | --
 |  | SHBG | -- | -- | -- | 54.8 (33)b | --
Multiple Dose Lo Loestrin Fe combination tabletc x 24 days | 24 | NE | 13900 (34) | 1.3 (0.7-3.0) | 84160 (41) | 917 (84) | 3510 (41)
 |  | EE | 71.3 (33) | 1.3 (0.3–2.0) | 621.3 (41) | 10.0 (92) | 25.9 (41)
 |  | SHBG | -- | -- | -- | 109 (38) | --
Multiple Dose Lo Loestrin Fe combination tabletc x 24 days and ethinyl estradiol alone tabletd x 2 days | 26 | EE | 49.9 (34) | 1.3 (0.7–3.0) | 403.6 (50) | -- | --
Cmax = Maximum plasma concentration (pg/mL); tmax = Time of Cmax (h); AUC0-24h = Area under plasma concentration versus time curve from 0 to 24 hours (pg·h/mL); Cmin = Minimum plasma concentration (pg/mL); Cavg = Average plasma concentration = AUC0-24h/24 (pg/mL)
Percent CV = Coefficient of Variation (percent); SHBG = Sex hormone binding globulin (nmol/L)
aThe median (range) is reported for tmax
bThe Cmin concentration reported for SHBG is the pre-dose concentration
cLo Loestrin Fe combination tablets contain 1 mg norethindrone acetate and 10 mcg ethinyl estradiol
dLo Loestrin Fe ethinyl estradiol alone tablets contain 10 mcg ethinyl estradiol

Food Effect:
Lo Loestrin Fe tablets may be administered without regard to meals.

Administration of food with a single-dose of a Lo Loestrin Fe combination tablet did not affect the maximum concentration of norethindrone and increased the extent of absorption by 24 percent; it decreased the maximum concentration of ethinyl estradiol by 23 percent and did not affect the extent of absorption.

Administration of food with a single-dose of a Lo Loestrin Fe ethinyl estradiol alone tablet decreased the maximum concentration of ethinyl estradiol by 31 percent and did not affect the extent of absorption.

Distribution
Volume of distribution of norethindrone and ethinyl estradiol ranges from 2 to 4 L/kg. Plasma protein binding of both steroids is extensive (>95 percent); norethindrone binds to both albumin and SHBG, whereas ethinyl estradiol binds only to albumin. Although ethinyl estradiol does not bind to SHBG, it induces SHBG synthesis.

Metabolism
Norethindrone undergoes extensive biotransformation, primarily via reduction, followed by sulfate and glucuronide conjugation. The majority of metabolites in the circulation are sulfates, with glucuronides accounting for most of the urinary metabolites. A small amount of norethindrone acetate is metabolically converted to ethinyl estradiol.

Ethinyl estradiol is also extensively metabolized, both by oxidation and by conjugation with sulfate and glucuronide. Sulfates are the major circulating conjugates of ethinyl estradiol and glucuronides predominate in urine. The primary oxidative metabolite is 2-hydroxy ethinyl estradiol, formed by the CYP3A4 isoform of cytochrome P450. Part of the first-pass metabolism of ethinyl estradiol is believed to occur in gastrointestinal mucosa. Ethinyl estradiol may undergo enterohepatic circulation.

Excretion
Norethindrone and ethinyl estradiol are excreted in both urine and feces, primarily as metabolites. Plasma clearance values for norethindrone and ethinyl estradiol are similar (approximately 0.4 L/hr/kg). Elimination half-lives of norethindrone and ethinyl estradiol following administration of 1 mg norethindrone acetate/10 mcg ethinyl estradiol tablets are approximately 10 hours and 16 hours, respectively.

Specific populations
The pharmacokinetics of Lo Loestrin Fe in presence of renal or hepatic impairment has not been evaluated [see Use in Specific Populations (8.6) and (8.7)].

13 NONCLINICAL TOXICOLOGY

13.1 Carcinogenesis, Mutagenesis, Impairment of Fertility

[See Warnings and Precautions (5.2, 5.3)]

14 CLINICAL STUDIES

In a one year (thirteen 28-day cycles) multicenter open-label clinical trial, 1,270 women 18 to 35 years of age, were studied to assess the efficacy of Lo Loestrin Fe, completing the equivalent of 12,482 28-day evaluable cycles of exposure. The racial demographic of all enrolled women was: Caucasian (74.9 percent), African-American (11.8 percent), Hispanic (9.8 percent), Asian (1.3 percent), and Other (2.2 percent). Women with body mass index (BMI) greater than 35 kg/m^2 were excluded from the study. The weight range for those women treated was 89 to 260 lbs., with a mean weight of 150 lbs. Among the women in the trial, 51 percent had not used hormonal contraception immediately prior to enrolling in this study. Of treated women, 13.7 percent were lost to follow-up, 10.7 percent discontinued due to an adverse event, and 8.9 percent discontinued by withdrawing their consent.

The pregnancy rate (Pearl Index [PI]) in women 18 to 35 years of age was 2.92 pregnancies per 100 women-years of use (95 percent confidence interval 1.94 – 4.21), based on 28 pregnancies that occurred after the onset of treatment and extending through the 7 days following the last dose of Lo Loestrin Fe. Cycles in which conception did not occur, but which included the use of backup contraception, were not included in the calculation of the PI. The PI includes women who did not take the drug correctly.

16 HOW SUPPLIED/STORAGE AND HANDLING

16.1 How Supplied

Lo Loestrin® Fe (norethindrone acetate and ethinyl estradiol tablets, ethinyl estradiol tablets and ferrous fumarate tablets) is available in blister cards (dispensers) containing 28 tablets:

NDC 0430-0420-14 Cartons of 5 blister cards (dispensers)

NDC 0430-0420-60 Cartons of 30 blister cards (dispensers)

Each blister card (28 tablets) contains in the following order:

- 24 blue, round tablets (active) imprinted with “WC” on one side and “421” on the other and each containing 1 mg norethindrone and 10 mcg ethinyl estradiol
- 2 white, hexagonal tablets (active) imprinted with “WC” on one side and “422” on the other and each containing 10 mcg ethinyl estradiol
- 2 brown, round tablets (non-hormonal placebo) imprinted with “WC” on one side and “624” on the other and each containing 75 mg ferrous fumarate

16.2 Storage Conditions

Store at 25º C (77º F); excursions permitted to 15 - 30º C (59 - 86º F) [see USP Controlled Room Temperature].

Keep this drug and all drugs out of the reach of children.

17 PATIENT COUNSELING INFORMATION

- Counsel patients that cigarette smoking increases the risk of serious cardiovascular events from COC use, and that women who are over 35 years old and smoke should not use COCs.
- Counsel patients that Lo Loestrin Fe does not protect against HIV infection (AIDS) and other sexually transmitted diseases.
- Counsel patients on the Warnings and Precautions associated with COCs.
- Counsel patients to take one tablet daily by mouth at the same time every day. Instruct patients what to do in the event pills are missed. See “What to Do if You Miss Pills” section in FDA-Approved Patient Labeling.
- Counsel patients to use a back-up or alternative method of contraception when enzyme inducers are used with Lo Loestrin Fe.
- Counsel patients who are breastfeeding or who desire to breastfeed that COCs may reduce breast milk production. This is less likely to occur if breastfeeding is well established.
- Counsel any patient who starts COCs postpartum, and who has not yet had a period, to use an additional method of contraception until she has taken a blue tablet for 7 consecutive days.
- Counsel patients that amenorrhea may occur. Rule out pregnancy in the event of amenorrhea in two or more consecutive cycles.

Distributed by:
AbbVie Inc.
North Chicago, IL 60064

Lo Loestrin Fe and its design are trademarks of Allergan Pharmaceuticals International Limited, an AbbVie company.

© 2025 AbbVie. All rights reserved.

Rev. 03/2025
2000017944

FDA-Approved Patient Labeling

Guide for Using Lo Loestrin Fe

WARNING TO WOMEN WHO SMOKE

Do not use Lo Loestrin Fe if you smoke cigarettes and are over 35 years old. Smoking increases your risk of serious cardiovascular side effects (heart and blood vessel problems) from birth control pills, including death from heart attack, blood clots or stroke. This risk increases with age and the number of cigarettes you smoke.

Birth control pills help to lower the chances of becoming pregnant when taken as directed. They do not protect against HIV infection (AIDS) and other sexually transmitted diseases.

What is Lo Loestrin Fe?

Lo Loestrin Fe is a birth control pill. It contains two female hormones, an estrogen called ethinyl estradiol, and a progestin called norethindrone acetate.

How well does Lo Loestrin Fe work?

Your chance of getting pregnant depends on how well you follow the directions for taking your birth control pills. The better you follow the directions, the less chance you have of getting pregnant.

Based on the results of one clinical study, about 2 to 4 out of 100 women may get pregnant during the first year they use Lo Loestrin Fe.

Women with a BMI above 35 kg/m^2 were not studied in the clinical trial, so it is not known how well Lo Loestrin Fe protects against pregnancy in such women. If you are overweight, discuss with your healthcare provider whether Lo Loestrin Fe is the best choice for you.

The following chart shows the chance of getting pregnant for women who use different methods of birth control. Each box on the chart contains a list of birth control methods that are similar in effectiveness. The most effective methods are at the top of the chart. The box on the bottom of the chart shows the chance of getting pregnant for women who do not use birth control and are trying to get pregnant.

How do I take Lo Loestrin Fe?

- Take one pill every day at the same time. If you miss pills you could get pregnant. This includes starting the pack late. The more pills you miss, the more likely you are to get pregnant.
- You may have spotting or light bleeding, or may feel sick to your stomach during the first few months of taking Lo Loestrin Fe. If you have spotting or light bleeding or feel sick to your stomach, do not stop taking the pill. The problem will usually go away. If it doesn't go away, check with your healthcare provider.
- Missing pills can also cause spotting or light bleeding, even when you take these missed pills later. On the days you take 2 pills to make up for missed pills, you could also feel a little sick to your stomach.
- If you have trouble remembering to take Lo Loestrin Fe, talk to your healthcare provider about how to make pill-taking easier or about using another method of birth control.
- If you have vomiting or diarrhea (within 3 to 4 hours after you take your pill), you should follow the instructions for “What to Do if You Miss Pills”.
- If you have any questions or are unsure about the information in this leaflet, call your healthcare provider.

Before you start taking Lo Loestrin Fe

1. Decide what time of day you want to take your pill. It is important to take it at the same time every day.

2. Look at your pill pack: The Lo Loestrin Fe pill pack has 24 "active" blue pills (with hormones) and 2 “active” white pills (with hormones) for Weeks 1, 2, 3 and part of Week 4. The pill pack also has 2 "reminder" brown pills (without hormones) for the last part of Week 4.

3. Find:

- Where on the pack to start taking pills,
- In what order to take the pills (follow the arrows), and
- The week numbers as shown in the picture above

4. Have ready at all times:

- Another kind of birth control (such as a condom and spermicide) to use as a back-up in case you miss pills
- An extra pill pack

When to start the first pack of Lo Loestrin Fe

1. Take the day label strip that starts with the first day of your period. (This is the day you start bleeding or spotting, even if it is almost midnight when the bleeding begins.)
2. Place the day label strip on the tablet dispenser over the area that has the days of the week (starting with Sunday) printed on the plastic.
3. Take the first blue pill of the first pack during the first 24 hours of your period.
4. You will not need to use a back-up method of birth control, because you are starting the pill at the beginning of your period. However, if you start Lo Loestrin Fe later than the first day of your period, or if you start after having a baby and you have not yet resumed your periods, you should use another method of birth control (such as a condom and spermicide) as a back-up method until you have taken 7 blue pills.

When You Switch from a Different Method of Hormonal Contraception

- When you switch from another birth control pill, start Lo Loestrin Fe on the first day you would have started your previous birth control pack.
- When you switch from a vaginal ring or skin patch, finish the 21 days of use, and wait 7 days after removal of the ring or patch before starting Lo Loestrin Fe.
- When you switch from a progestin-only pill, start Lo Loestrin Fe the next day.
- When you switch from an implant, start Lo Loestrin Fe on the day of implant removal.
- If you switch from an injectable contraceptive, start Lo Loestrin Fe on the day on which the next injection would be due.
- If you switch from an IUD, discuss with your healthcare provider when to start Lo Loestrin Fe.

What to do during the month

- Take one pill at the same time every day until the pack is empty.
  • Do not skip pills even if you are spotting or bleeding between monthly periods or feel sick to your stomach (nausea).
  • Do not skip pills even if you do not have sex very often.
- When you finish a pack of Lo Loestrin Fe, start the next pack on the day after your last brown “reminder" pill. Do not skip any days between packs.

What to do if you miss pills

Birth control pills may not be as effective if you miss any blue or white pills, especially if you miss the first few or the last few blue pills in a pack.

If you miss ONE blue pill, follow these steps:

- Take it as soon as you remember. Take the next pill at your regular time. This means you may take two pills in 1 day.
- You do not need to use a back-up birth control method if you have sex.

If you miss TWO blue pills in a row in Week 1 or Week 2 of your pack, follow these steps:

- Take
  1. Two pills on the day you remember and two pills the next day.
  2. One pill a day until you finish the pack.
- You could become pregnant if you have sex during the first 7 days after you restart your pills. You MUST use a non-hormonal birth control method (such as a condom and spermicide) as a back-up for those 7 days.

If you miss TWO pills (blue or white) in a row in Week 3 or Week 4 of your pack, follow these steps:

- Throw out the rest of the pill pack and start a new pack that same day.
- You may not have your period this month but this is expected. However, if you miss your period 2 months in a row, call your healthcare provider because you might be pregnant.
- You could become pregnant if you have sex during the first 7 days after you restart your pills. You MUST use a non-hormonal birth control method (such as a condom and spermicide) as a back-up for those 7 days after you restart your pills.

If you miss THREE OR MORE pills (blue or white) in a row at any time, follow these steps:

- Throw out the rest of the pill pack and start a new pack that same day.
- You may not have your period this month but this is expected. However, if you miss your period 2 months in a row, call your healthcare provider because you might be pregnant.
- You could become pregnant if you have sex on the days when you missed pills or during the first 7 days after restarting your pills. You MUST use a non-hormonal birth control method (such as a condom and spermicide) as a back-up the next time you have sex and for the first 7 days after you restart your pills.

If you forget either of the 2 brown "reminder" pills in Week 4, follow these steps:

- Throw away the pill you missed.
- Start a new pack on the same day you usually start a new pack.
- You do not need to use a back-up method of birth control.

If you are still not sure what to do about the pills you have missed:

- Use a back-up method of birth control anytime you have sex.
- Keep taking one pill each day until you can reach your healthcare provider.

Who should not take Lo Loestrin Fe?

Your healthcare provider will not give you Lo Loestrin Fe if you have:

- Ever had blood clots in your legs (deep vein thrombosis), lungs (pulmonary embolism), or eyes (retinal thrombosis)
- Ever had a stroke
- Ever had a heart attack
- Certain heart valve problems or heart rhythm abnormalities that can cause blood clots to form in the heart
- An inherited problem with your blood that makes it clot more than normal
- High blood pressure that medicine can't control
- Diabetes with kidney, eye, nerve, or blood vessel damage
- Ever had certain kinds of severe migraine headaches with aura, numbness, weakness or changes in vision
- Ever had breast cancer, which may be sensitive to female hormones
- Liver disease, including liver tumors
- Take any Hepatitis C drug combination containing ombitasvir/paritaprevir/ritonavir, with or without dasabuvir. This may increase levels of the liver enzyme “alanine aminotransferase” (ALT) in the blood.

Also, do not take birth control pills if you:

- Smoke and are over 35 years old
- Are allergic to anything in Lo Loestrin Fe

Birth control pills may not be a good choice for you if you have ever had jaundice (yellowing of the skin or eyes) caused by pregnancy, also called cholestasis of pregnancy.

Tell your healthcare provider if you have ever had any of the above conditions (your healthcare provider may recommend another method of birth control).

What else should I know about taking Lo Loestrin Fe?

Birth control pills do not protect you against any sexually transmitted disease, including HIV, the virus that causes AIDS.

Do not skip any pills, even if you do not have sex often.

If you miss a period, you could be pregnant. However, some women miss periods or have light periods on birth control pills, even when they are not pregnant. Contact your healthcare provider for advice if you:

- Think you are pregnant
- Miss one period and have not taken your birth control pills every day
- Miss two periods in a row

Birth control pills should not be taken during pregnancy. However, birth control pills taken by accident during pregnancy are not known to cause birth defects.

You should stop Lo Loestrin Fe at least four weeks before you have surgery and not restart it until at least two weeks after the surgery, due to an increased risk of blood clots.

If you are breastfeeding, consider another birth control method until you are ready to stop breastfeeding. Birth control pills that contain estrogen, like Lo Loestrin Fe, may decrease the amount of milk you make. A small amount of the pill's hormones pass into breast milk.

Tell your healthcare provider about all medicines and herbal products that you take. Some medicines and herbal products may make birth control pills less effective, including:

- barbiturates
- bosentan
- carbamazepine
- felbamate
- griseofulvin
- oxcarbazepine
- phenytoin
- rifampin
- St. John’s wort
- topiramate

Consider using another birth control method when you take medicines that may make birth control pills less effective.

Birth control pills may interact with lamotrigine, an anticonvulsant used for epilepsy. This may increase the risk of seizures, so your healthcare provider may need to adjust the dose of lamotrigine.

If you have vomiting or diarrhea, your birth control pills may not work as well. Use another birth control method, like a condom and spermicide, until you check with your healthcare provider.

If you are scheduled for any laboratory tests, tell your healthcare provider that you are taking birth control pills. Certain blood tests may be affected by birth control pills.

What are the most serious risks of taking Lo Loestrin Fe?

Like pregnancy, birth control pills increase the risk of serious blood clots, especially in women who have other risk factors, such as smoking, obesity, or age greater than 35. It is possible to die from a problem caused by a blood clot, such as a heart attack or a stroke.

Some examples of serious blood clots are blood clots in the:

- Legs (deep vein thrombosis)
- Lungs (pulmonary embolus)
- Eyes (loss of eyesight)
- Heart (heart attack)
- Brain (stroke)

A few women who take birth control pills may get:

- High blood pressure
- Gallbladder problems
- Rare cancerous or noncancerous liver tumors

All of these events are uncommon in healthy women.

Call your healthcare provider right away if you have:

- Persistent leg pain
- Sudden shortness of breath
- Sudden blindness, partial or complete
- Severe pain or pressure in your chest
- Sudden, severe headache unlike your usual headaches
- Weakness or numbness in an arm or leg, or trouble speaking
- Yellowing of the skin or eyeballs

What are the common side effects of birth control pills?

The most common side effects of birth control pills are:

- Spotting or bleeding between menstrual periods
- Nausea
- Breast tenderness
- Headache

These side effects are usually mild and usually disappear with time.

Less common side effects are:

- Acne
- Less sexual desire
- Bloating or fluid retention
- Blotchy darkening of the skin, especially on the face
- High blood sugar, especially in women who already have diabetes
- High fat (cholesterol, triglyceride) levels in the blood
- Depression, especially if you have had depression in the past. Call your healthcare provider immediately if you have any thoughts of harming yourself
- Problems tolerating contact lenses
- Weight gain

This is not a complete list of possible side effects. Talk to your healthcare provider if you develop any side effects that concern you. You may report side effects to the FDA at 1-800-FDA-1088.

No serious problems have been reported from a birth control pill overdose, even when accidentally taken by children.

Do birth control pills cause cancer?

It is not known if hormonal birth control pills cause breast cancer. Some studies, but not all, suggest that there could be a slight increase in the risk of breast cancer among current users with longer duration of use.

If you have breast cancer now, or have had it in the past, do not use hormonal birth control because some breast cancers are sensitive to hormones.

Women who use birth control pills may have a slightly higher chance of getting cervical cancer. However, this may be due to other reasons such as having more sexual partners.

What should I know about my period when taking Lo Loestrin Fe?

When you take Lo Loestrin Fe you may have bleeding and spotting between periods, called unscheduled bleeding. Approximately half of the women who use Lo Loestrin Fe have unscheduled bleeding or spotting in the first months of use, and about one-third of users continue to have unscheduled bleeding or spotting after one year of use. If the unscheduled bleeding or spotting is heavy or lasts for more than a few days, you should discuss this with your healthcare provider.

What if I miss my scheduled period when taking Lo Loestrin Fe?

It is not uncommon to miss your period. However, if you go two or more months in a row without a period, or you miss your period after a month where you did not take all your pills correctly, call your healthcare provider because you may be pregnant. Also notify your healthcare provider if you have symptoms of pregnancy such as morning sickness or unusual breast tenderness. Stop taking Lo Loestrin Fe if you are pregnant.

What if I want to become pregnant?

You may stop taking the pill whenever you wish. Consider a visit with your healthcare provider for a pre-pregnancy checkup before you stop taking the pill.

General Advice about Lo Loestrin Fe

Your healthcare provider prescribed Lo Loestrin Fe for you. Please do not share Lo Loestrin Fe with anyone else. Keep Lo Loestrin Fe out of the reach of children.

If you have concerns or questions, ask your healthcare provider. You may also ask your pharmacist for a more detailed label written for healthcare professionals.

Distributed by:
AbbVie Inc.
North Chicago, IL 60064

Lo Loestrin Fe and its design are trademarks of Allergan Pharmaceuticals International Limited, an AbbVie company.

© 2025 AbbVie. All rights reserved.

Rev. 03/2025
2000017944

PACKAGE LABEL

PRINCIPAL DISPLAY PANEL

NDC 0430-0420-14
Rx only
Lo Loestrin® Fe
(norethindrone acetate and ethinyl estradiol tablets,
ethinyl estradiol tablets and ferrous fumarate tablets)
1 mg/10 mcg and 10 mcg
Lo Loestrin® Fe provides
26 days of active therapy
5 blister cards of 28 tablets each
Allergan

PACKAGE LABEL

PRINCIPAL DISPLAY PANEL

NDC 0430-0420-95
Lo Loestrin® Fe
(norethindrone acetate and ethinyl estradiol tablets,
ethinyl estradiol tablets and ferrous fumarate tablets)
1 mg/10 mcg and 10 mcg
Lo Loestrin® Fe provides
26 days of active therapy
Rx only
Physician’s Sample – Not For Sale
This package contains 1 blister card of 28 tablets each
Allergan